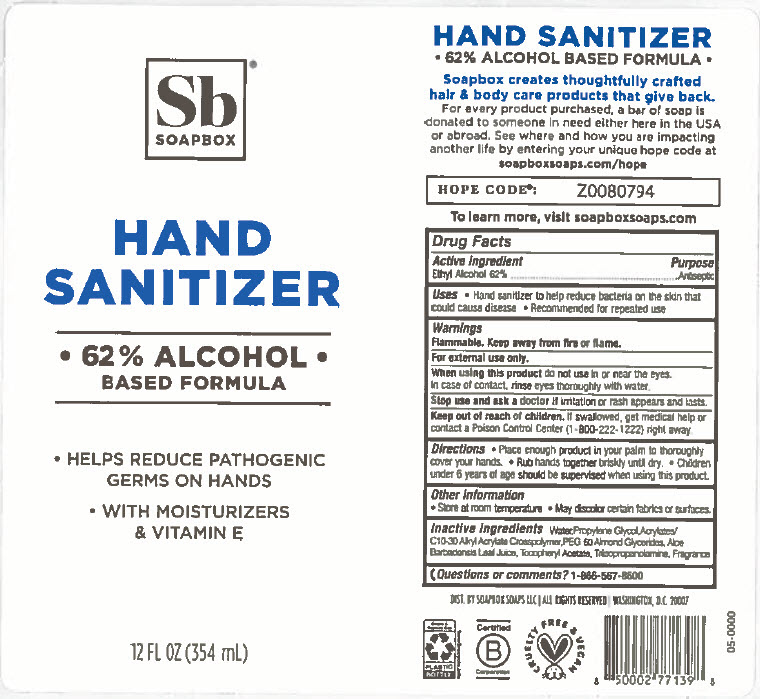 DRUG LABEL: Hand Sanitizer 
NDC: 75115-772 | Form: GEL
Manufacturer: Soapbox Soaps, LLC
Category: otc | Type: HUMAN OTC DRUG LABEL
Date: 20200417

ACTIVE INGREDIENTS: ALCOHOL 62 mL/100 mL
INACTIVE INGREDIENTS: PROPYLENE GLYCOL; WATER; PEG-60 ALMOND GLYCERIDES; ALOE VERA LEAF; .ALPHA.-TOCOPHEROL ACETATE; TRIISOPROPANOLAMINE; CARBOMER INTERPOLYMER TYPE B (ALLYL PENTAERYTHRITOL CROSSLINKED)

Hand Sanitizer
62% Alcohol based formula

Drug Facts

Active Ingredient

Ethyl Alcohol 62%

Purpose

Antiseptic

Uses

- for hand washing to decrease bacteria on the skin
- recommended for repeated use

Warnings

Flammable. Keep away from fire or flame.

For external use only.

When using this product do not use in or near the eyes.

In case of contact, rinse eyes thoroughly with water.

Stop use and ask a doctor if irritation and rash appears and lasts.

Keep Out of reach of children. If swallowed get medical help or contact poison control center (1-800-222-1222) right away.

Directions

- Place enough product in your palm to thoroughly cover your hands.
- Rub hands together briskly until dry.
- Children under 6 years of age should be supervised when using this product.

Other Information

- store at room temperature
- may discolor certain fabrics

Inactive Ingredients

Water, Propylene Glycol, Acrylates/C10-3- Alkyl Acrylate Crosspolymer, Peg-60 Almond Glycerides, Aloe Barbadensis Leaf Juice, Triisopropanolamine, Fragrance

Questions or Comments ?

1-866-567-8600

DIST. BY SOAPBOX SOAPS LLC | WASHINGTON, D.C. 20007

PRINCIPAL DISPLAY PANEL - 354 mL Bottle Label

SOAPBOX®

HAND
SANITIZER

• 62% ALCOHOL •
BASED FORMULA

- HELPS REDUCE PATHOGENIC
  GERMS ON HANDS
- WITH MOISTURIZERS
  & VITAMIN E

12 FL OZ (354 mL)